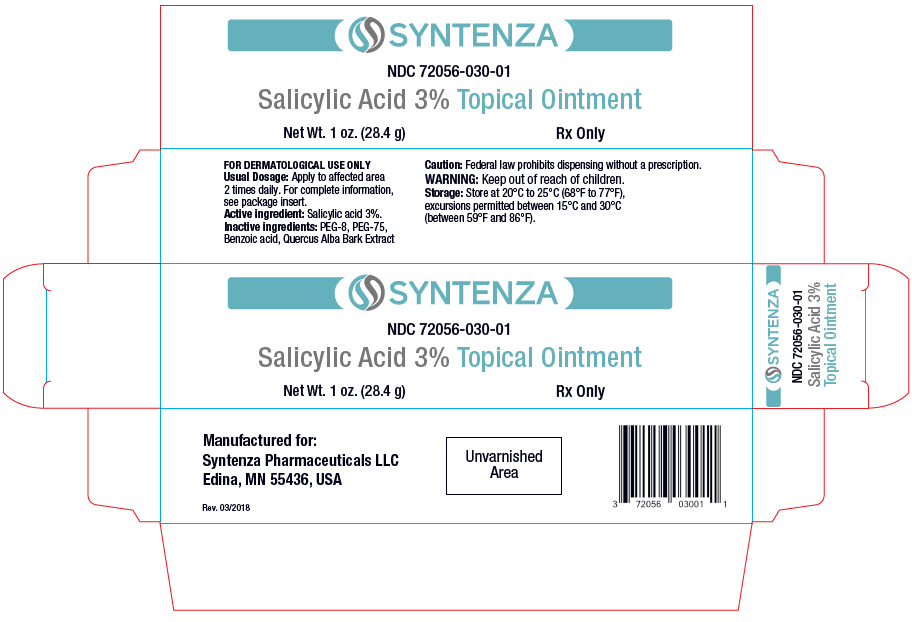 DRUG LABEL: SALICYLIC ACID
NDC: 72056-030 | Form: OINTMENT
Manufacturer: Syntenza Pharmaceuticals LLC
Category: prescription | Type: HUMAN PRESCRIPTION DRUG LABEL
Date: 20181016

ACTIVE INGREDIENTS: SALICYLIC ACID 30 mg/1 g
INACTIVE INGREDIENTS: Benzoic Acid

Salicylic Acid 3% Topical Ointment

Rx Only

Prescribing Information

DESCRIPTION

Salicylic Acid 3% topical ointment contains 30 mg salicylic acid per gram in a base containing: PEG-8, PEG-75, Benzoic acid and Quercus Alba Bark Extract.

CLINICAL PHARMACOLOGY

The mechanism of action of Salicylic Acid 3% topical ointment is not known. While the following animal data are available, their clinical significance is unknown. It has been demonstrated that Salicylic Acid 3% topical ointment significantly reduces methicillin-resistant Staphylococcus aureus (MRSA) protected by biofilms in wounds using porcine models. In addition, Salicylic Acid 3% topical ointment stimulates re-epithelialization of second-degree burns in porcine models.

CLINICAL STUDIES

A randomized, double-blind, placebo-controlled study evaluated the rate of wound re-epithelialization. Four partial-thickness wounds (2×2 cm & 0.2 mm deep) were created under local anesthesia on the thighs of 13 normal, healthy, male volunteers with an electrokeratome. Salicylic Acid 3% topical ointment substantially increased the rate of re-epithelialization by 63% over the vehicle alone (p<0.01) and 77% over untreated control (p<0.005).

INDICATIONS AND USAGE

An external treatment for the inflammation and irritation associated with many common forms of dermatitis, including certain eczematoid conditions. These conditions include complications associated with pyodermas. Indicated also in the treatment of insect bites, burns and fungal infections.

CONTRAINDICATIONS

Salicylic Acid 3% topical ointment is contraindicated for use in those patients who are hypersensitive to topical polyethylene glycols.

PRECAUTIONS

For external use only. Not to be used in eyes.

DRUG INTERACTIONS

It is not known if Salicylic Acid 3% topical ointment interacts with other topical medications applied to the treatment area. The use of Salicylic Acid 3% topical ointment with other topical drugs has not been studied.

ADVERSE REACTIONS

Salicylic Acid 3% topical ointment is generally well tolerated and non-irritating. A small percentage of patients may experience a temporary burning sensation upon application of the ointment.

DOSAGE AND ADMINISTRATION

Patients should be advised to follow these step-by-step instructions for application of Salicylic Acid 3% topical ointment:

Hands should be washed thoroughly.

When using tubes, the tip of the tube should not come into contact with the area to be treated; the tube should be recapped tightly after each application.

If applying with a cotton-tipped applicator, which is recommended, use once and discard.

Salicylic Acid 3% topical ointment should be applied twice a day for best results.

Gently rinse the area to be treated with saline or water and then pat dry. Salicylic Acid 3% topical ointment can be applied directly to the wound or placed on dry gauze and then placed on the wound. Wet-Packs or Wet-To-Dry Dressings are not recommended since they will dilute the ointment and decrease its effectiveness. Salicylic Acid 3% topical ointment is designed to provide moisture to the wound.

Spread a generous quantity of Salicylic Acid 3% topical ointment evenly over the desired area to yield a thin continuous layer of approximately 1/8 of an inch of thickness. There may be a mild warming sensation, or slight burning, to the treated area for 3-5 minutes after application. If irritation occurs or symptoms persist after 10 days, discontinue use and consult your physician.

Try to keep the area being treated clean and exposed to air when possible. Apply an appropriate dressing to shield the area from clothes or exposure to water or dirt.

If there is no improvement in the wound within 7 days, consult your physician for further evaluation of the wound. If there is no response to the ointment at all, then the wound should be re-evaluated for other contributing factors to the wound healing process.

PEDIATRIC USE

Safety and effectiveness in pediatric patients has not been established.

HOW SUPPLIED

30 g tube | NDC 72056-030-01

STORAGE AND HANDLING

Store at 20°C to 25°C (68°F to 77°F), excursions permitted between 15°C and 30°C (between 59°F and 86°F). Brief exposure to temperatures up to 40°C (104°F) may be tolerated provided the mean kinetic temperature does not exceed 25°C (77°F); however, such exposure should be minimized.

Manufactured for:
Syntenza Pharmaceuticals LLC
Edina, MN 55436, USA

Rev. 06/18

PRINCIPAL DISPLAY PANEL - 28.4 g Tube Carton

SYNTENZA

NDC 72056-030-01

Salicylic Acid 3% Topical Ointment

Net Wt. 1 oz. (28.4 g)

Rx Only